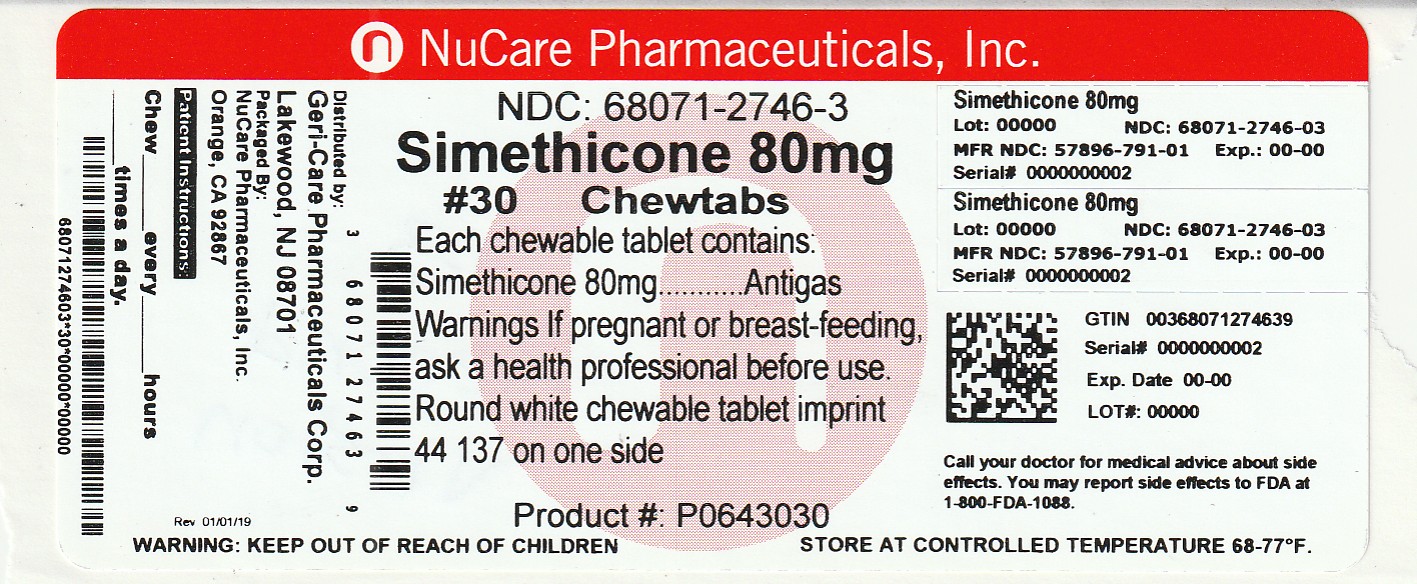 DRUG LABEL: SIMETHICONE
NDC: 68071-2746 | Form: TABLET, CHEWABLE
Manufacturer: NuCare Pharmaceuticals,Inc.
Category: otc | Type: HUMAN OTC DRUG LABEL
Date: 20250224

ACTIVE INGREDIENTS: DIMETHICONE 80 mg/1 1
INACTIVE INGREDIENTS: CELLULOSE, MICROCRYSTALLINE; DEXTRATES; SILICON DIOXIDE; TRICALCIUM PHOSPHATE; STARCH, CORN; CROSPOVIDONE; MAGNESIUM STEARATE; SUCRALOSE

gc 791

Active ingredient (in each tablet)

Simethicone 80 mg

Purpose

Anti-Gas

Uses

relieves pressure, bloating, and fullness
commonly referred to as gas

Warnings

If pregnant or breast feeding, ask a health professional before use.

Keep out of reach of children.

Directions

- chew or crush tablet completely before swallowing
- adults and children 12 years and over: take 1-2 tablets as needed after meals and at bedtime.

Do not exceed 6 tablets in 24 hours except under the advice and supervision of a doctor.

- children under 12 years: ask a doctor

Other information

- each tablet contains: calcium 65 mg
- Tamper Evident: Do not use if imprinted seal under cap is missing or broken
- store at room temperature, 15°C - 30°C (59˚F - 86˚F)
- protect from moisture

Inactive ingredients

cellulose, corn starch, crospovidone, dextrates hydrated, flavor,
magnesium stearate, silica, sucralose, calcium phosphate.

Questions or comments?

1-800-540-3765